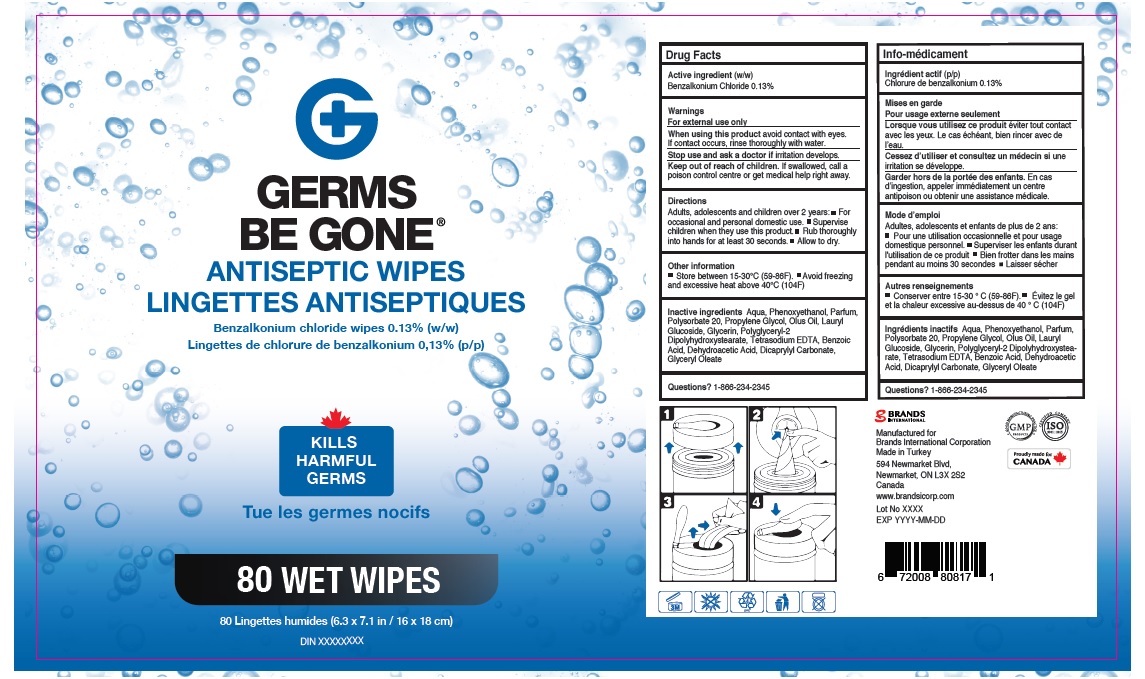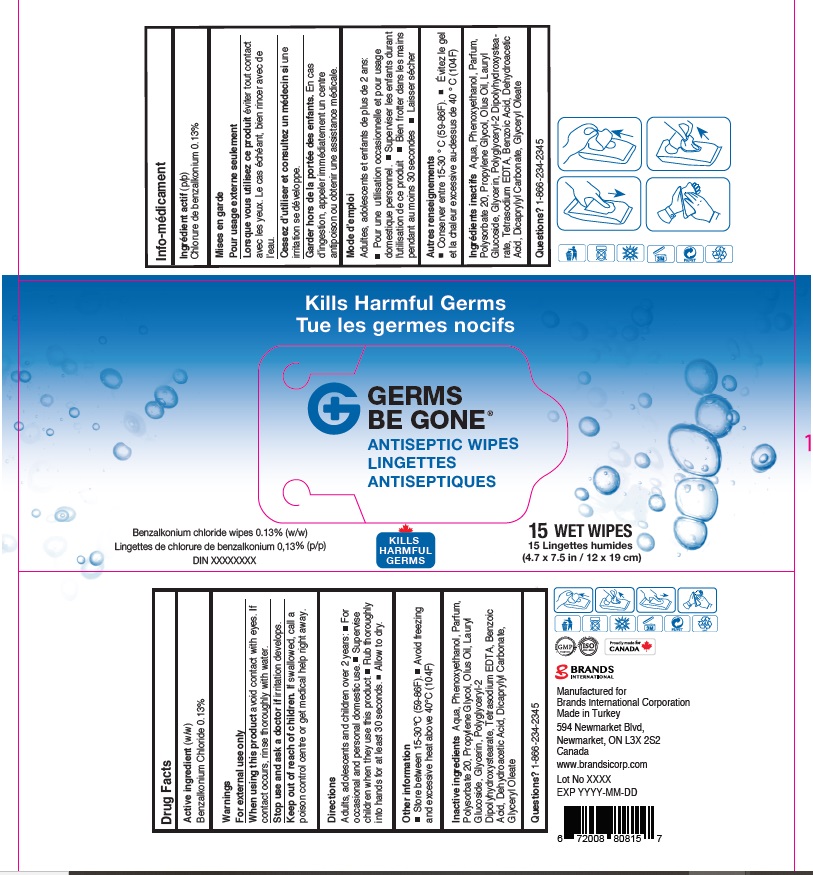 DRUG LABEL: Germs Be Gone Antiseptic wipes
NDC: 50157-522 | Form: CLOTH
Manufacturer: Brands International corporation
Category: otc | Type: HUMAN OTC DRUG LABEL
Date: 20210814

ACTIVE INGREDIENTS: BENZALKONIUM CHLORIDE 0.13 1/100 1
INACTIVE INGREDIENTS: EDETATE SODIUM; BENZOIC ACID; PROPYLENE GLYCOL; DEHYDROACETIC ACID; POLYSORBATE 20; GLYCERIN; PHENOXYETHANOL; WATER; LAURYL GLUCOSIDE; POLYGLYCERYL-2 DIPOLYHYDROXYSTEARATE; GLYCERYL OLEATE; DICAPRYLYL CARBONATE

Germs Be Gone Antiseptic wipes. Scented

Active Ingredient(s)

Benzalkonium Chloride 0.13%

Purpose

Kills (harmful) bacteria/germs to provide antiseptic cleansing

Use

Kills (harmful) bacteria/germs.

Warnings

For extenal use only.

WHEN USING

Avoid contact with eyes. if contact occurs, rinse thoroughly with water.

STOP USE

If irritation develops.

Keep out of reach of children. If swallowed, get medical help or contact a Poison Control Center right away.

Directions

- Adults, adolescents and children over 2 years:
- For occasional and personal domestic use.
- Supervise children when they use this product.
- Rub thoroughly into hands for at least 30 seconds.
- Allow to dry.

Other information

- store between 15-30C (59-86F)
- Avoid freezing and excessive heat above 40C (104F)

Inactive ingredients

Water, Glycerin, Parfume, Dicaprylyl Carbonate, Glyceryl Oleate, Lauryl glucoside, Olus oil, Polyglyceryl-2Dipolyhydroxystearate

Phenoxyethanol, Polysorbate 20, Benzoic acid, Tetrasodium EDTA, Dehydroacetic acid, Propylene glycol